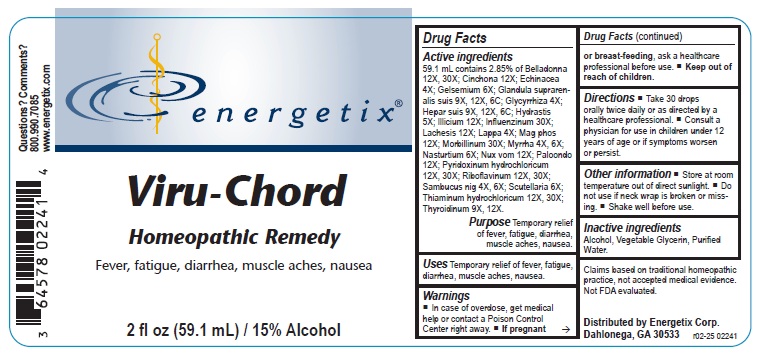 DRUG LABEL: Viru-Chord
NDC: 64578-0128 | Form: LIQUID
Manufacturer: Energetix Corporation
Category: homeopathic | Type: HUMAN OTC DRUG LABEL
Date: 20251222

ACTIVE INGREDIENTS: ATROPA BELLADONNA 12 [hp_X]/1 mL; CINCHONA OFFICINALIS BARK 12 [hp_X]/1 mL; ECHINACEA ANGUSTIFOLIA 4 [hp_X]/1 mL; GELSEMIUM SEMPERVIRENS ROOT 6 [hp_X]/1 mL; SUS SCROFA ADRENAL GLAND 9 [hp_X]/1 mL; GLYCYRRHIZA GLABRA 4 [hp_X]/1 mL; PORK LIVER 9 [hp_X]/1 mL; GOLDENSEAL 5 [hp_X]/1 mL; STAR ANISE 12 [hp_X]/1 mL; INFLUENZA A VIRUS A/BRISBANE/10/2010 (H1N1) HEMAGGLUTININ ANTIGEN (MDCK CELL DERIVED, PROPIOLACTONE INACTIVATED) 30 [hp_X]/1 mL; INFLUENZA A VIRUS A/BRISBANE/10/2010 (H1N1) NEURAMINIDASE ANTIGEN (MDCK CELL DERIVED, PROPIOLACTONE INACTIVATED) 30 [hp_X]/1 mL; INFLUENZA A VIRUS A/SOUTH AUSTRALIA/55/2014 (H3N2) HEMAGGLUTININ ANTIGEN (MDCK CELL DERIVED, PROPIOLACTONE INACTIVATED) 30 [hp_X]/1 mL; INFLUENZA A VIRUS A/SOUTH AUSTRALIA/55/2014 (H3N2) NEURAMINIDASE ANTIGEN (MDCK CELL DERIVED, PROPIOLACTONE INACTIVATED) 30 [hp_X]/1 mL; INFLUENZA B VIRUS B/UTAH/9/2014 HEMAGGLUTININ ANTIGEN (MDCK CELL DERIVED, PROPIOLACTONE INACTIVATED) 30 [hp_X]/1 mL; INFLUENZA B VIRUS B/UTAH/9/2014 NEURAMINIDASE ANTIGEN (MDCK CELL DERIVED, PROPIOLACTONE INACTIVATED) 30 [hp_X]/1 mL; LACHESIS MUTA VENOM 12 [hp_X]/1 mL; ARCTIUM LAPPA ROOT 4 [hp_X]/1 mL; MAGNESIUM PHOSPHATE, DIBASIC TRIHYDRATE 12 [hp_X]/1 mL; MEASLES VIRUS 30 [hp_X]/1 mL; MYRRH 4 [hp_X]/1 mL; NASTURTIUM OFFICINALE 6 [hp_X]/1 mL; STRYCHNOS NUX-VOMICA SEED 12 [hp_X]/1 mL; LARREA TRIDENTATA LEAF 12 [hp_X]/1 mL; PYRIDOXINE HYDROCHLORIDE 12 [hp_X]/1 mL; RIBOFLAVIN 12 [hp_X]/1 mL; SAMBUCUS NIGRA FLOWERING TOP 4 [hp_X]/1 mL; SCUTELLARIA LATERIFLORA 6 [hp_X]/1 mL; THIAMINE HYDROCHLORIDE 12 [hp_X]/1 mL; THYROID, BOVINE 9 [hp_X]/1 mL
INACTIVE INGREDIENTS: WATER; ALCOHOL; GLYCERIN

Viru-Chord

ACTIVE INGREDIENT

Active ingredients59.1 mL contains 2.85% of: Belladonna 12X, 30X, Cinchona 12X, Echinacea 4X, Gelsemium 6X, Glandula Suprarenalis Suis 9X, 12X, 6C, Glycyrrhiza 4X, Hepar Suis 9X, 12X, 6C, Hydrastis 5X, Illicium 12X, Influenzinum 30X, Lachesis 12X, Lappa 4X, Mag Phos 12X, Morbillinum 30X, Myrrha 4X, 6X, Nasturtium 6X, Nux Vomica 12X, Paloondo 12X, Pyridoxinum Hydrochloricum 12X, 30X, Riboflavinum 12X, 30X, Sambucus Nig 4X, 6X, Scutellaria 6X, Thiaminum Hydrochloricum 12X, 30X, Thyroidinum 9X, 12X.

Claims based on traditional homeopathic practice, not accepted medical evidence. Not FDA evaluated.

INDICATIONS AND USAGE

UsesTemporary relief of fever, fatigue, diarrhea, muscle aches, nausea.

Warnings

• In case of overdose, get medical help or contact a Poison Control Center right away.

If pregnant or breast feeding,ask a healthcare professional before use.

Keep out of reach of children.

DOSAGE AND ADMINISTRATION

Take 30 drops orally twice daily or as directed by a healthcare professional.

Consult a physician for use in children under 12 years of age or if symptoms worsen or persist.

Directions

• Take 30 drops orally twice daily or as directed by a healthcare professional.

• Consult a physician for use in children under 12 years of age or if symptoms worsen or persist.

Other information

• Store at room temperature out of direct sunlight.

• Do not use if neck wrap is broken or missing.

• Shake well before use.

Inactive ingredients

Alcohol, Vegetable Glycerin, Purified Water.

QUESTIONS

Distributed by Energetix Corp.

Dahlonega, GA 30533

Questions? 800.990.7085

www.energetix.com

PACKAGE LABEL

energetix

Viru-Chord

Homeopathic Remedy

Fever, fatigue, diarrhea, muscle aches, nausea.

2 fl oz (59.1 mL) / 15% Alcohol

PURPOSE

PurposeTemporary relief of fever, fatigue, diarrhea, muscle aches, nausea.